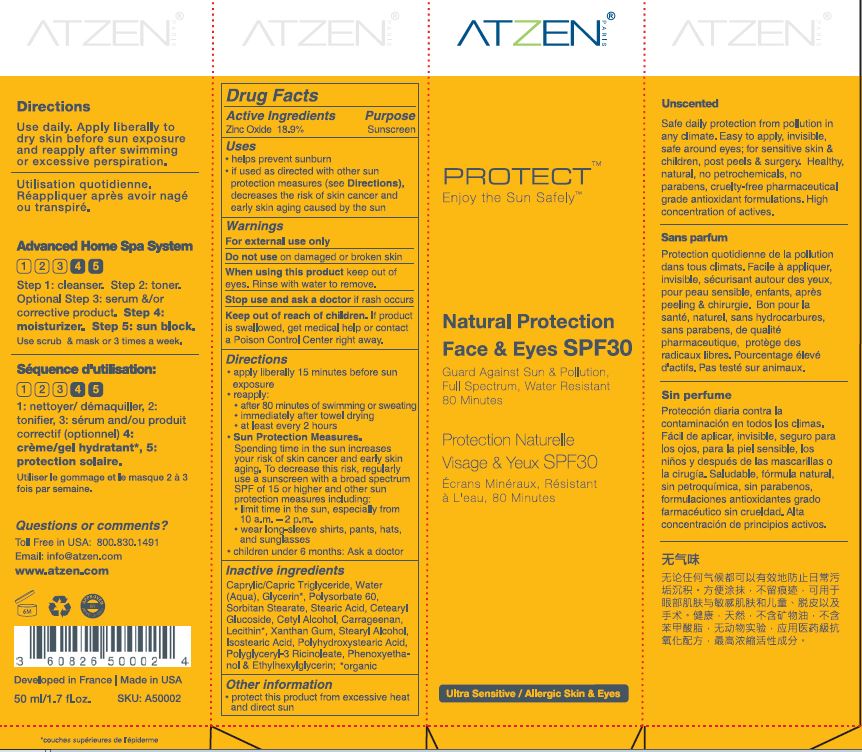 DRUG LABEL: Natural Protection Face and Eyes SPF 30
NDC: 62742-4162 | Form: CREAM
Manufacturer: ALLURE LABS INC
Category: otc | Type: HUMAN OTC DRUG LABEL
Date: 20171218

ACTIVE INGREDIENTS: ZINC OXIDE 189 mg/1 mL
INACTIVE INGREDIENTS: WATER; CAPRYLIC/CAPRIC/LAURIC TRIGLYCERIDE; STEARIC ACID; GLYCERIN; POLYSORBATE 60; PEG-20 SORBITAN STEARATE; PHENOXYETHANOL; CETEARYL GLUCOSIDE; CETYL ALCOHOL; CARRAGEENAN; XANTHAN GUM; STEARYL ALCOHOL; POLYHYDROXYSTEARIC ACID (2300 MW); ISOSTEARIC ACID; POLYGLYCERYL-3 RICINOLEATE; ETHYLHEXYLGLYCERIN; LECITHIN, SOYBEAN

Drug Facts

Active Ingredients:

Zinc Oxide - 18.9%

Purpose: Sunscreen

INDICATIONS AND USAGE

Uses: Helps prevent sunburn. If used as directed with other sun protection measures (see Direction), decreases the risk of skin cancer and early skin aging caused by the sun.

WARNINGS

For external use only.

Do not use on damaged or broken skin.

WHEN USING

Keep out of eyes. Rinse with water to remove.

Stop use and ask a doctor if rash occurs.

KEEP OUT OF REACH OF CHILDREN

If product is swallowed, get medical help or contact a Poison Control Center right away.

Directions:

- Apply liberally 15 minutes prior to sun exposure.
- Reapply: after 80 minutes of swimming or sweating. Immediately after towel drying. At least every 2 hours.
- Sun Protection Measures. Spending time in the sun increases your risk of skin cancer and early skin aging. To decrease the risk, regularly use a sunscreen with a broad spectrum SPF of 15 or higher and other sun protection measures including:
- limit time in sun sun, especially from 10 am - 2 pm.
- wear long-sleeve shirts, pants, hats and sunglasses.
- Children under 6 months: Ask a doctor.

INACTIVE INGREDIENT

Caprilic/Capric Triglyceride, Water (Aqua), Stearic Acid, Glycerin, Polysorbate 60, Sorbitan Stearate, Cetearyl Glucoside, Cetyl Alcohol, Carrageenan, Lecithin, Xanthan Gum, Stearyl Alcohol, Isostearic Acid, Polyhydroxystearic Acid, Polyglyceryl-3 Ricinoleate, Phenoxyethanol, Ethylhexylglycerin.

OTHER SAFETY INFORMATION

Protect this product from excessive heat and direct sun.

QUESTIONS

Call toll free 1-800 830-1491 in the USA.

info@atzen.com

PACKAGE LABEL

Toll free in USA: 800.830.1491

Email: info@atzen.com

www.atzen.com

Developed in France. Made in USA.